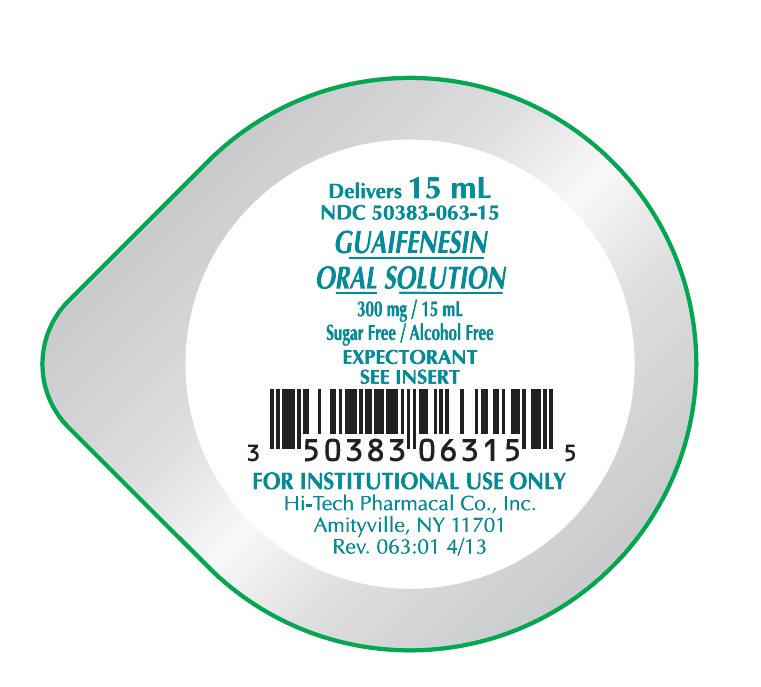 DRUG LABEL: Guaifenesin
NDC: 50383-063 | Form: SOLUTION
Manufacturer: Akorn
Category: otc | Type: HUMAN OTC DRUG LABEL
Date: 20221115

ACTIVE INGREDIENTS: GUAIFENESIN 100 mg/5 mL
INACTIVE INGREDIENTS: ACESULFAME POTASSIUM; ASPARTAME; HYPROMELLOSE 2910 (4000 MPA.S); MENTHOL, UNSPECIFIED FORM; METHYLPARABEN; POTASSIUM SORBATE; WATER; ANHYDROUS CITRIC ACID

Drug Facts

Active ingredient

Each 5 mL (1 teaspoonful) contains:

Guaifenesin ................................................ 100 mg

Inactive ingredients

Acesulfame K, artificial cherry & vanilla flavor, aspartame, hypromellose, menthol, methylparaben, potassium sorbate, purified water. Citric acid may be used to adjust pH.

Purpose

Expectorant

Uses

Helps loosen phlegm (mucus) and thin bronchial secretions to make coughs more productive.

Warnings

Ask a doctor before use if you have

- cough that occurs with too much phlegm (mucus)
- cough that lasts or is chronic such as occurs with smoking, asthma, chronic bronchitis, or emphysema

Stop use and ask a doctor if

- cough lasts more than 7 days, comes back, or is accompanied by fever, rash, or persistent headache. These could be signs of a serious condition.
- you are hypersensitive to any of the ingredients

If pregnant or breast-feeding,

ask a health professional before use.

Keep out of reach of children.

In case of overdose, get medical help or contact a Poison Control Center right away.

Professional Note: Guaifenesin has been shown to produce a color interference with certain clinical laboratory determinations of 5-hydroxyindoleacetic acid (5-HIAA) and vanillylmandelic acid (VMA).

Directions

Follow dosage below or use as directed by a physician.

- do not take more than 6 doses in any 24-hour period

age | dose
adults and children 12 years and over | 10 to 20 mL (2 to 4 teaspoonfuls) every 4 hours
children 6 years to under 12 years | 5 to 10 mL (1 to 2 teaspoonfuls) every 4 hours
children 2 to under 6 years of age | 2.5 to 5 mL (1/2 to 1 teaspoonful) every 4 hours
children under 2 years of age | ask a doctor

How Supplied:

Guaifenesin Oral Solution is a clear viscous liquid with a slight cherry odor supplied in the following oral dosage forms: 5 mL unit dose, 10 mL unit dose, 15 mL unit dose in trays of 10 and 4 fl. oz. (118 mL) bottle

Phenylketonurics: contains phenylalanine 8.4 mg per teaspoonful (5 mL)

STORAGE

Keep tightly closed. Store at controlled room temperature, 20°-25°C (68°-77°F). [See USP] Protect from light.

Questions or comments?

Call 1-800-262-9010.

Hi-Tech Pharmacal Co., Inc.

Amityville, NY 11701

Rev.063:01 4/13

MG #29850

Package/Label Principal Display Panel

Delivers 15 mL

NDC 50383-063-15

GUAIFENESIN ORAL SOLUTION

300 mg/15 mL

Sugar Free/Alcohol Free

EXPECTORANT

SEE INSERT

FOR INSTITUTIONAL USE ONLY

Hi-Tech Pharmacal Co., Inc.

Amityville, NY 11701

Rev. 063:01 4/13